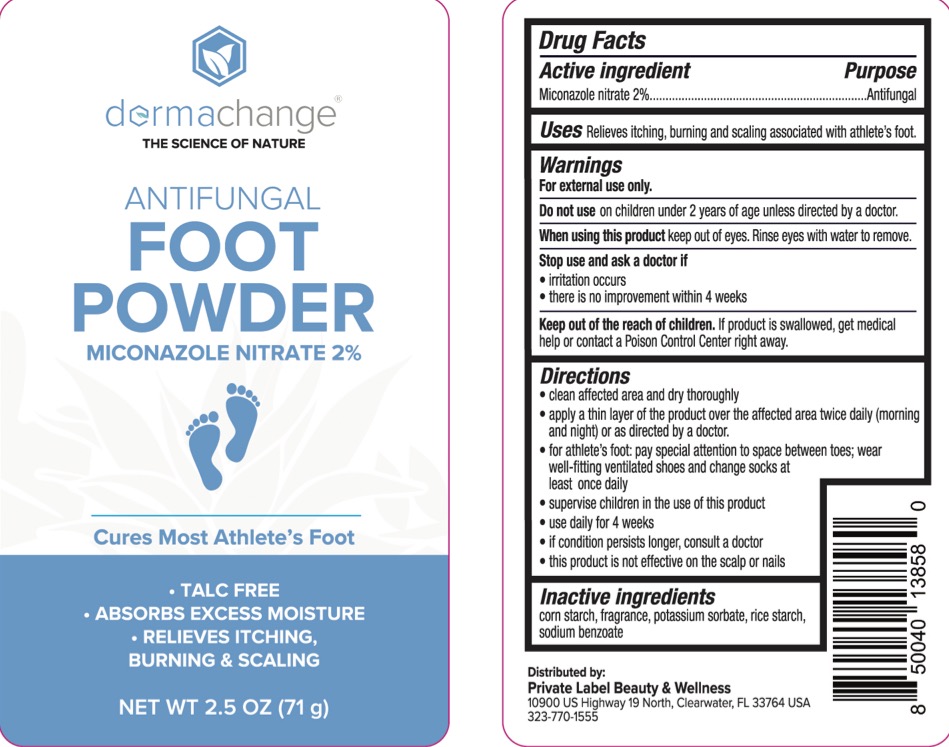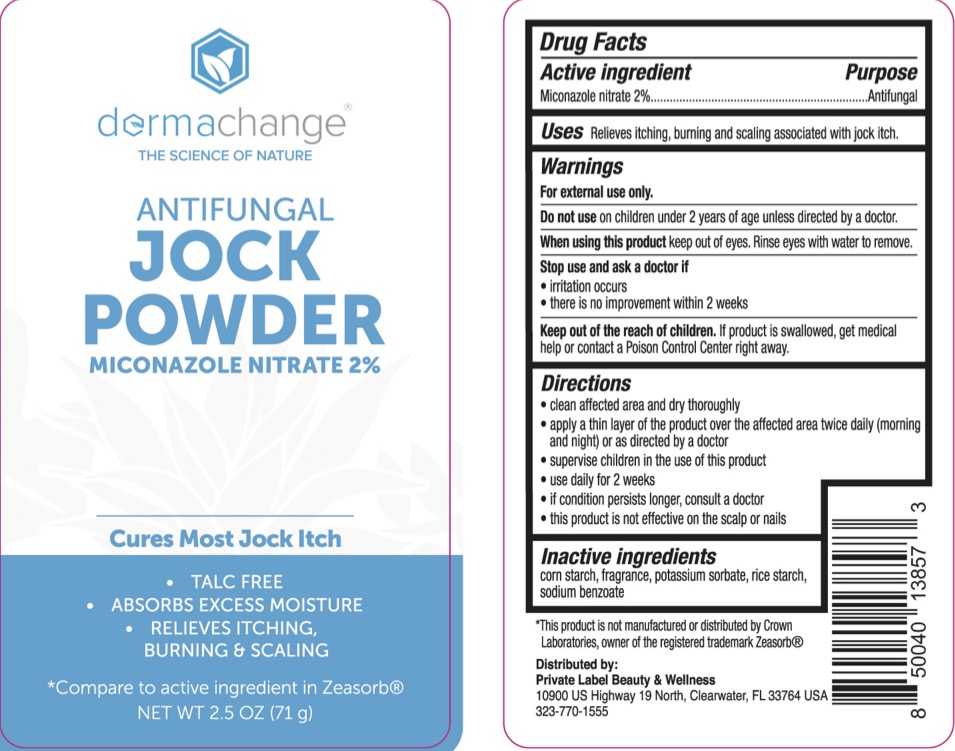 DRUG LABEL: Dermachange Jock
NDC: 83520-961 | Form: POWDER
Manufacturer: Private label Beauty and Wellness
Category: otc | Type: HUMAN OTC DRUG LABEL
Date: 20240305

ACTIVE INGREDIENTS: MICONAZOLE NITRATE 2 g/100 g
INACTIVE INGREDIENTS: SODIUM BENZOATE; STARCH, CORN; POTASSIUM SORBATE; STARCH, RICE

Dermachange Foot and Jock Powder, 2% Miconazole Nitrate

ACTIVE INGREDIENT

Miconazole Nitrate 2%

PURPOSE

Antifungal

INDICATIONS AND USAGE

For the cure of athlete's foot and jock itch. Relieves itching and chafing associated with jock itch.

WARNINGS

For external use only. Do not use on children under 2 years of age unless directed by a doctor or for diaper rash. When using thisproduct avoid contact with the eyes. Stop use and ask a doctor if irritation occurs or if there is no improvement within 2 weeks.

KEEP OUT OF REACH OF CHILDREN

If swallowed, get medical help or contact a Poison Control Center right away.

DOSAGE AND ADMINISTRATION

Jock Powder

Cleanse the affected area and dry thoroughly. Apply a thin layer of the product over the affected area twice daily or as directed by a doctor.

Supervise children in the use of this product.

Use daily for 2 weeks.

If the condition persists, consult a doctor.

This product is not effective on the scalp or nails.

Foot Powder

Cleanse the affected area and dry thoroughly. Apply a thin layer of the product over the affected area twice daily or as directed by a doctor.

For athlete's foot: pay special attention to space between toes; wear well-fitting ventilated shoes and change socks at least once daily.

Supervise children in the use of this product.

Use daily for 4 weeks.

If the condition persists, consult a doctor.

This product is not effective on the scalp or nails.

INACTIVE INGREDIENT

Corn Starch, Fragrance, Potassium Sorbate, Rice Starch, Sodium Benzoate.

PACKAGE LABEL

Dermachange Jock Powder, NDC 83520-961-21

Dermachange Foot Powder, NDC 83520-961-02